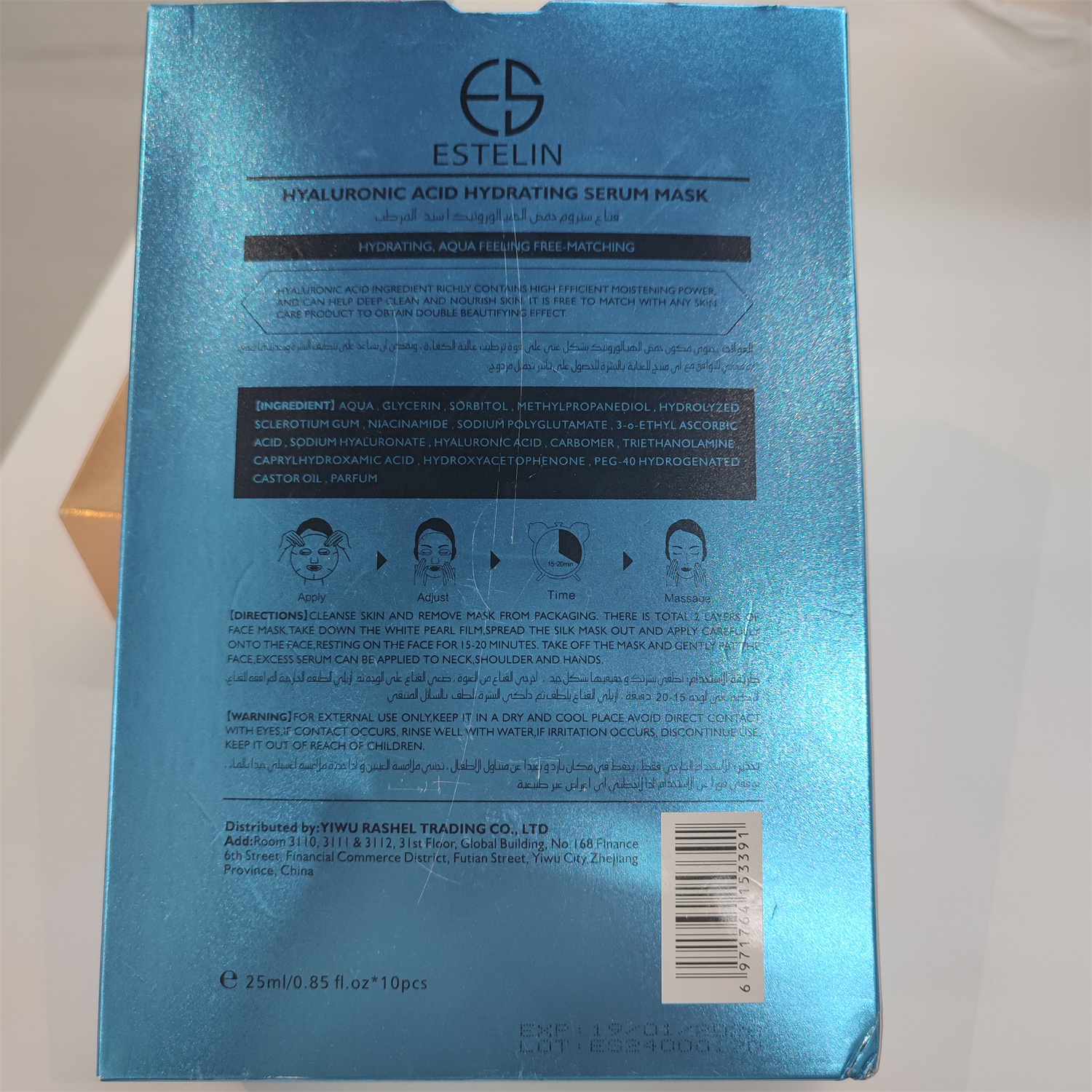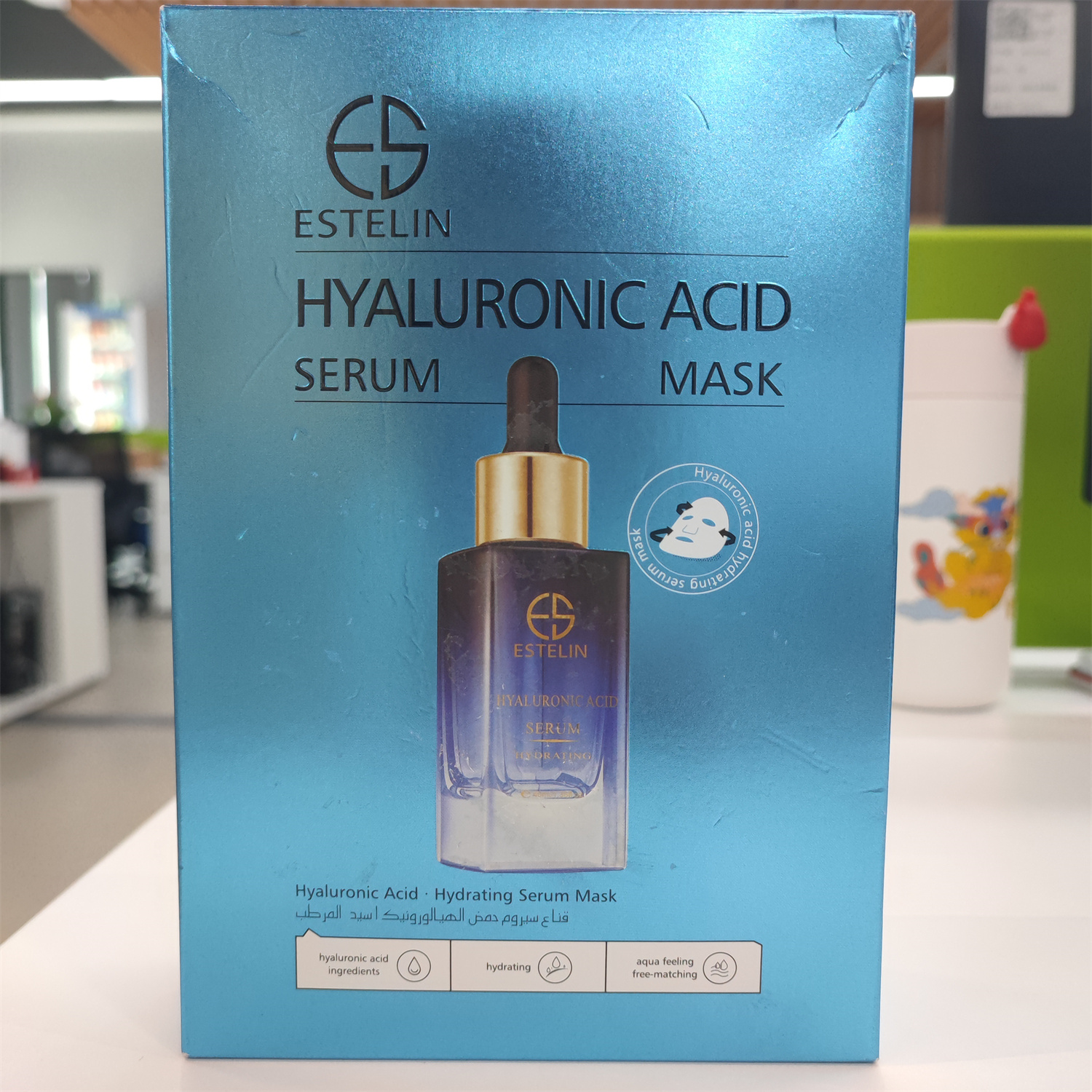 DRUG LABEL: ESTELIN HYALURONIC ACID SERUM MASK
NDC: 84716-003 | Form: DRESSING
Manufacturer: Shenzhen Boyang E-commerce Co.
Category: otc | Type: HUMAN OTC DRUG LABEL
Date: 20241014

ACTIVE INGREDIENTS: SORBITOL 7.23 g/250 mL; METHYLPROPANEDIOL 2.41 g/250 mL; GLYCERIN 7.23 g/250 mL
INACTIVE INGREDIENTS: WATER 230.905 mL/250 mL

ACTIVE INGREDIENTS

GLYCERIN 3%

SORBITOL 3%
METHYLPROPANEDIOL 1%

PURPOSE

HYDRATING, AQUA FEELINIG FREE-MATCHING
HYALURONIC ACID INGREDIENT RICHLY CONTNNS HIGH EFFICIENT MOISTENING POWER,AND CAN HELP DEEP GLEAN AND NOURISH SKIN, IT IS FREE TO MATCH WITH ANY SKIN CARE PRODUCT TO OBTAIN DOUBLE BEAUTIFYINIG EFFECT.

Uses

CLEANSE SKIN AND REMOVE MASK FROM PACKAGING. THERE IS TOTAL 2 LAYERS OF FACE MASK, TAKE DOWN THE WHITE PEARL FILM,SPREAD THE SILK MASK OUT AND APPLY CAREFULLY ONTO THE FACE, RESTING ON THE FACE FOR 15-20 MINUTES, TAKE OFF THE MASK AND GENTLY PAT THE FACE,EXCESS SERUM CAN BE APPLIED TO NECK,SHOULDER AND HANDS.

Warnings

FOR EXTERNAL USE ONLY.

KEEP IT IN A DRY AND COOL PLACE AVOID DIREET CONTACT WITH EYES, IF CONTACT OCCURS, RINSE WELL WITH WATER,IF IRRITATION OCCURS,

DISCONTINUE USE KEEP IT OUT OF REACH OF CHILDREN.

Stop use and ask a doctor if

lt is recommended to have a skin test (inside the wrist orbehind the ear) before use.If you feel uncomfortable,please stop using it.

Do not use

on damaged or broken skin

Keep out of reach of children

Please place it out of the reach of infants；If swallowed, get medical help or contact a Poison Control Center right away

When using this product

For external use only

keep out of eyes. Rinse with water to remove.

INACTIVE INGREDIENT SECTON

WATER

uses and storage method

USES:

CLEANSE SKIN AND REMOVE MASK FROM PACKAGING. THERE IS TOTAL 2 LAYERS OF FACE MASK, TAKE DOWN THE WHITE PEARL FILM,SPREAD THE SILK MASK OUT AND APPLY CAREFULLY ONTO THE FACE, RESTING ON THE FACE FOR 15-20 MINUTES, TAKE OFF THE MASK AND GENTLY PAT THE FACE,EXCESS SERUM CAN BE APPLIED TO NECK,SHOULDER AND HANDS.

FOR EXTERNAL USE ONLY.

KEEP IT IN A DRY AND COOL PLACE AVOID DIREET CONTACT WITH EYES, IF CONTACT OCCURS, RINSE WELL WITH WATER,IF IRRITATION OCCURS,

DISCONTINUE USE KEEP IT OUT OF REACH OF CHILDREN.